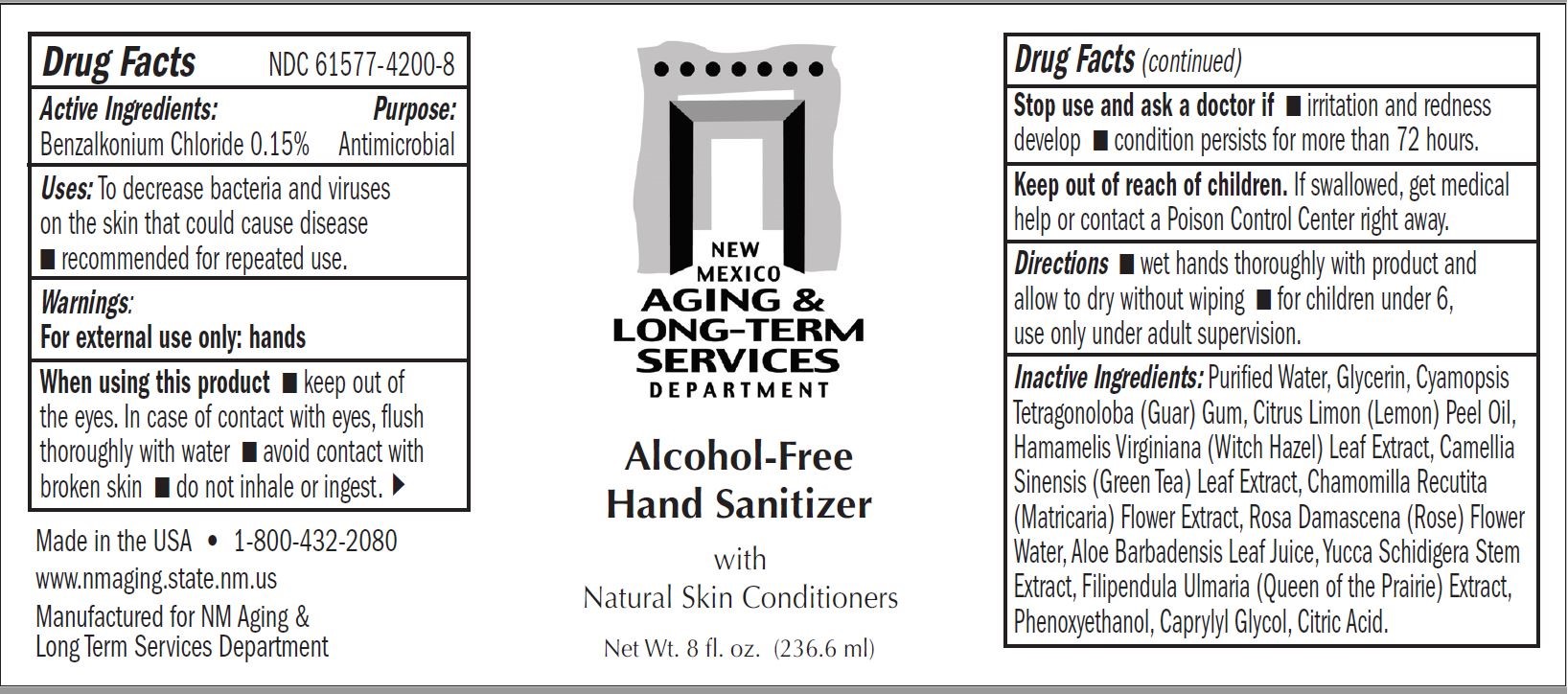 DRUG LABEL: Ne Mexico Aging Long Term Services Department Hand Sanitizer
NDC: 61577-4200 | Form: GEL
Manufacturer: Sombra Cosmetics
Category: otc | Type: HUMAN OTC DRUG LABEL
Date: 20210903

ACTIVE INGREDIENTS: BENZALKONIUM CHLORIDE 0.15 g/100 g
INACTIVE INGREDIENTS: WATER; GLYCERIN; CITRIC ACID MONOHYDRATE; GUAR GUM; LEMON OIL; WITCH HAZEL; ALOE VERA LEAF; ROSA DAMASCENA FLOWER; CHAMOMILE; YUCCA SCHIDIGERA STEM; FILIPENDULA RUBRA WHOLE; GREEN TEA LEAF; PHENOXYETHANOL; CAPRYLYL GLYCOL

New Mexico Aging Long-Term Services Department Alcohol Free Hand Sanitizer

Active Ingredients

Benzalkonium Chloride 0.15%

Uses

To decrease bacteria and viruses on the skin that could cause disease. Recommended for repeated use.

Warnings

For external use only: hands.

Do Not Use

avoid contact with broken skin. Do not inhale or ingest. Children under 6, use only
under adult supervision. Not recommended for infants.

When Using

When using this product, keep out of the eyes. In case of contact with eyes, flush thoroughly with water.

Stop Use

Stop use if irritation and redness develop or if condition persists for more than 72 hours.

Keep out of reach of childrenn

If swallowed, get medical help or contact a Poison Control Center right away.

Directions

Wet hands thoroughly with product and allow to dry without wiping. For children inder 6, use only under adult supervision.

Storage and Handling

Store away from oxidizing agents. Do not store above 100 C.

Inactive ingredients

Purified water, glycerin, cyamopsis tetragonoloba (Guar) gum, citrus limon (lemon) peel oil, hamamelis virginiana (witch hazel) leaf extract, camellia sinensis (green tea) leaf extract, champmilla recutita (matricaria) flower extract, rosa damascena (rose) flower waterr, aloe barbadensis leaf juice, yucca schidigera stem extract, filipendula ulmaria (queen of the prairie) extract, phenoxyethanol, caprylyl glyol, citric acid

Purpose

Anitmicrobial